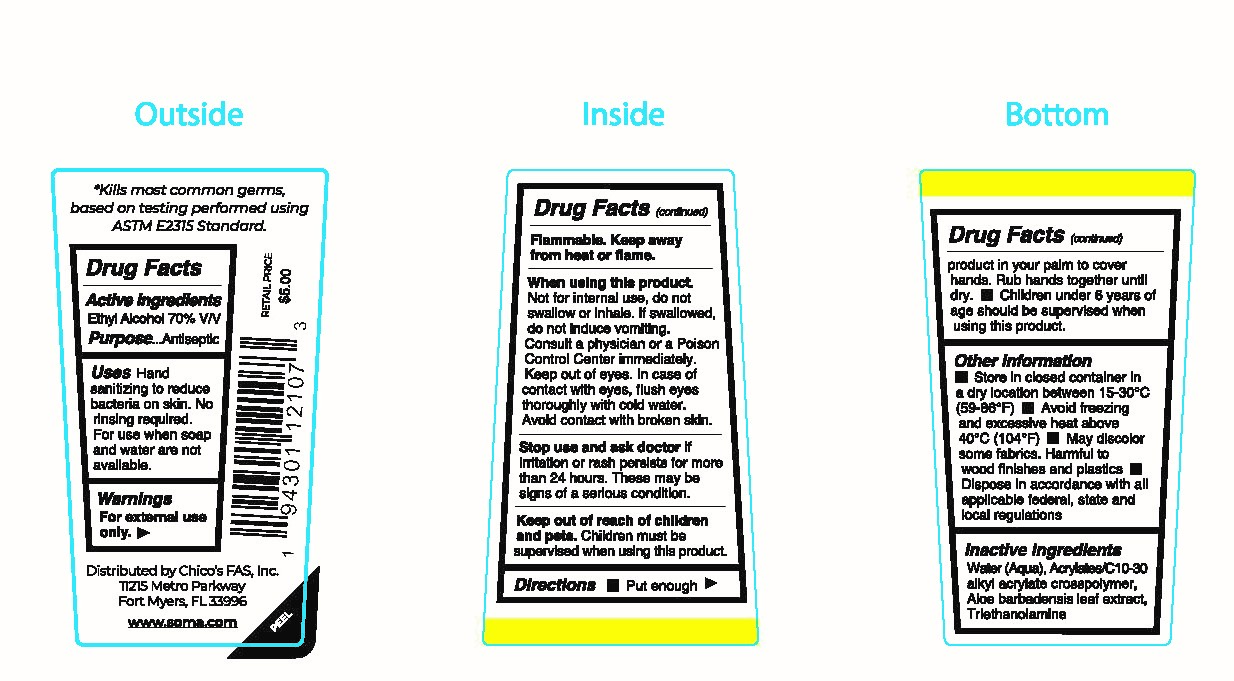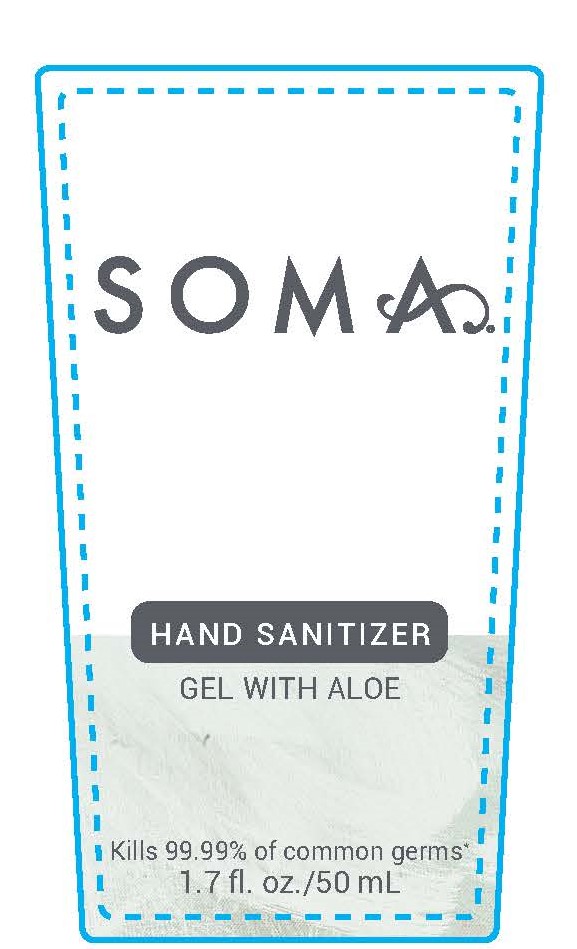 DRUG LABEL: Hand Sanitizer
NDC: 65657-071 | Form: GEL
Manufacturer: Chico's FAS INC
Category: otc | Type: HUMAN OTC DRUG LABEL
Date: 20201207

ACTIVE INGREDIENTS: ALCOHOL 70 mL/100 mL
INACTIVE INGREDIENTS: TROLAMINE; CARBOMER INTERPOLYMER TYPE A (55000 CPS); ALOE VERA LEAF; WATER

Hand Sanitizer

Active Ingredient(s)

Alcohol 70% v/v. Purpose: Antiseptic

Purpose

Antiseptic, Hand Sanitizer

Use

Hand sanitizing to reduce bacteria on skin. No rinsing required. For use when soap and water are not available.

Warnings

For external use only. Flammable. Keep away from heat or flame

Do not use

- in children less than 2 months of age
- on open skin wounds

When using this product. Not for internal use, do not swallow or inhale. If swallowed, do not induce vomiting. Consult a physician or a Poison Control Center immediately. Keep out of eyes. In case of thoroughly with cold water. Avoid contact with broken skin.

Stop use and ask doctor if irritation or rash persists for more than 24 hours. These may be signs of a serious condition. Keep out of reach of children

Keep out of reach of children and pets. Children must be supervised when using this product

Directions

- Put enough product in your palm to cover hands. Rub hands together until dry.
- Children under 6 years of age should be supervised when using this product.

Other information

- Store between 15-30C (59-86F)
- Avoid freezing and excessive heat above 40C (104F)
- May discolor some fabrics. Harmful to wood finishes and plastics.
- Dispose in accordance wiht all applicable federal, state and local regulations

Inactive ingredients

Water (Aqua), Acrylates/C10-30 alkyl acrylate crosspolymer, Aloe barbadensis leaf extract, Triethanolamine

Package Label - Principal Display Panel

50 mL NDC:65657-071-01